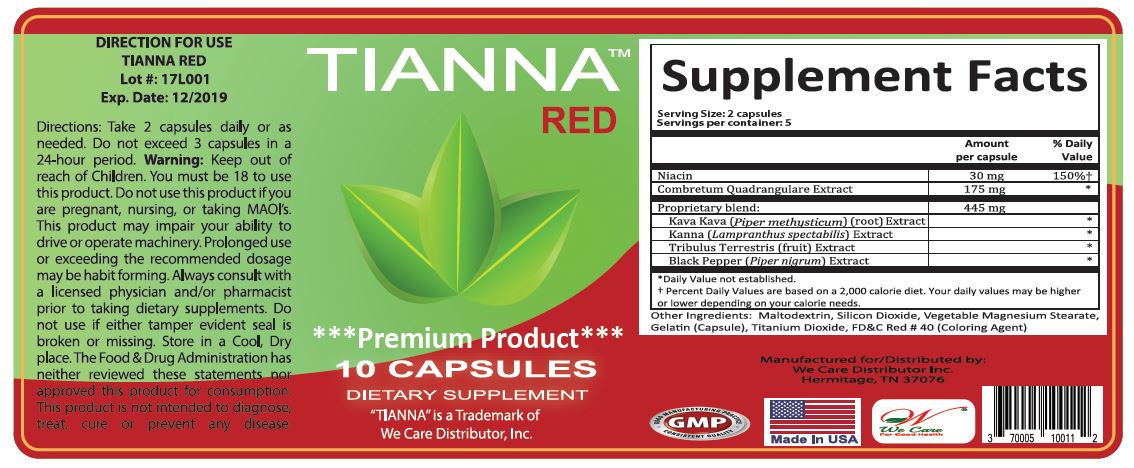 DRUG LABEL: TIANNA RED
NDC: 70005-100 | Form: CAPSULE
Manufacturer: We Care Distributor Inc.
Category: other | Type: DIETARY SUPPLEMENT
Date: 20180307

ACTIVE INGREDIENTS: NIACIN 30 mg/1 1; COMBRETUM MICRANTHUM WHOLE 175 mg/1 1; MESEMBRYANTHEMUM TORTUOSUM WHOLE 175 mg/1 1; TRIBULUS TERRESTRIS FRUIT 100 mg/1 1; WHITE PEPPER 30 mg/1 1; MACROPIPER METHYSTICUM ROOT 140 mg/1 1
INACTIVE INGREDIENTS: MALTODEXTRIN; SILICON DIOXIDE; MAGNESIUM STEARATE; GELATIN; TITANIUM DIOXIDE; FD&C RED NO. 40

TIANNA

STATEMENT OF IDENTITY

The Food & Drug Administration has neither reviewed these statements nor approved this product for consumption

HEALTH CLAIM

This product is not intended to diagnose, treat, cure, or prevent any disease.

WARNINGS

This product may impair your ability to drive or operate machinery. Prolonged use or exceeding the recommended dosage may be habit forming.

Do not use this product if you are pregnant, nursing, or taking MAOI’s.

Always consult your physician prior to taking this or any dietary supplements

SAFE HANDLING WARNING

Storage: Keep in a cool dry place. Do not use if tamper evident seal is broken or missing.

Keep out of reach of children
In bottle desiccant required.

Directions:

- Take 2 capsules daily or as needed
- Do not exceed 3 capsules in a 24-hour period.
- You must be 18 to use this product.

Bottle with Red Label - NDC# 70005-100-11

Bottles:
10 capsules/bottle.
2 capsules/serving
Servings per Container: 5